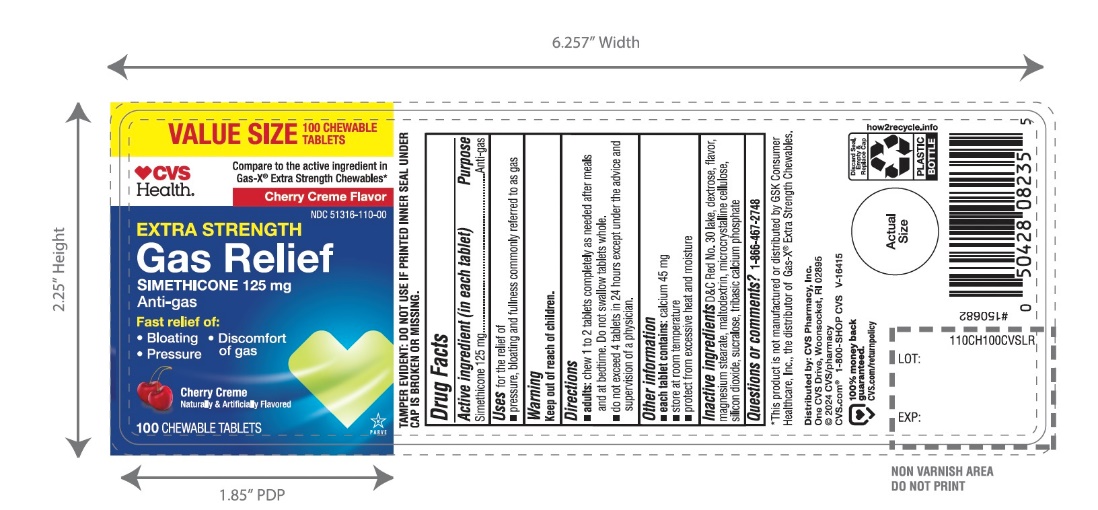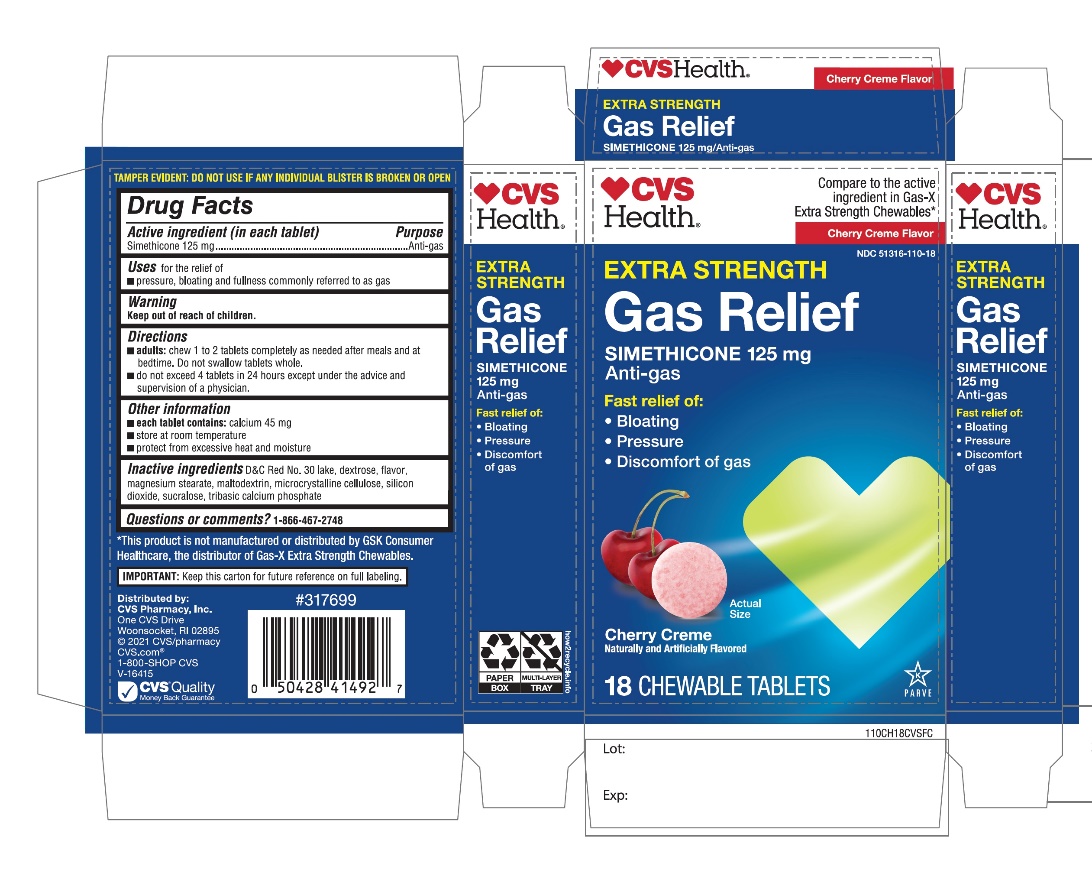 DRUG LABEL: CVS PHARMACY

NDC: 51316-110 | Form: TABLET, CHEWABLE
Manufacturer: CVS
Category: otc | Type: HUMAN OTC DRUG LABEL
Date: 20251208

ACTIVE INGREDIENTS: DIMETHICONE, UNSPECIFIED 125 mg/1 1
INACTIVE INGREDIENTS: D&C RED NO. 30; DEXTROSE, UNSPECIFIED FORM; MAGNESIUM STEARATE; MALTODEXTRIN; MICROCRYSTALLINE CELLULOSE; SILICON DIOXIDE; SUCRALOSE; TRIBASIC CALCIUM PHOSPHATE

CVS Extra Strength Gas Relief

Active ingredient (in each tablet)

Simethicone 125 mg

Purpose

Anti-gas

Uses

For the relief of

- pressure, bloating and fullness commonly referred to as gas

Directions

- adults: chew 1 to 2 tablets completely as needed after meals and at bedtime. Do not swallow tablets as whole.
- do not exceed 4 tablets in 24 hours except under the advice and supervision of a physician.

Other information

- each tablets contains:calcium 45 mg
- store at room temperature
- protect from excessive heat and moisture

DO NOT USE IF ANY INDVIDUAL BLISTER IS BROKEN OR OPEN

Inactive ingredients

D&C Red No. 30, dextrose, flavor, magnesium stearate, maltodextrin, microcrystalline cellulose, silicon dioxide, sucralose, tribasic calcium phosphate.

Questions or comments?

1-866-467-2748

Principal Display Panel

NDC 51316-110-18

*Compare to the active ingredient in Cas-X®Extra Strength

Extra Strength

Gas Relief

Simethicone / Antigas

For Fast Relief of Pressure, Bloating & Discomfort

Cherry Creme Flavor

Naturally and Artificially Flavored

18 CHEWABLE TABLETS

K PAREVE

*This product is not manufactured or distributed by GSK Consumer Healthcare, Inc. the distributor of Gas-X®Extra strength.

IMPORTANT:Keep this carton for future reference on full labeling.